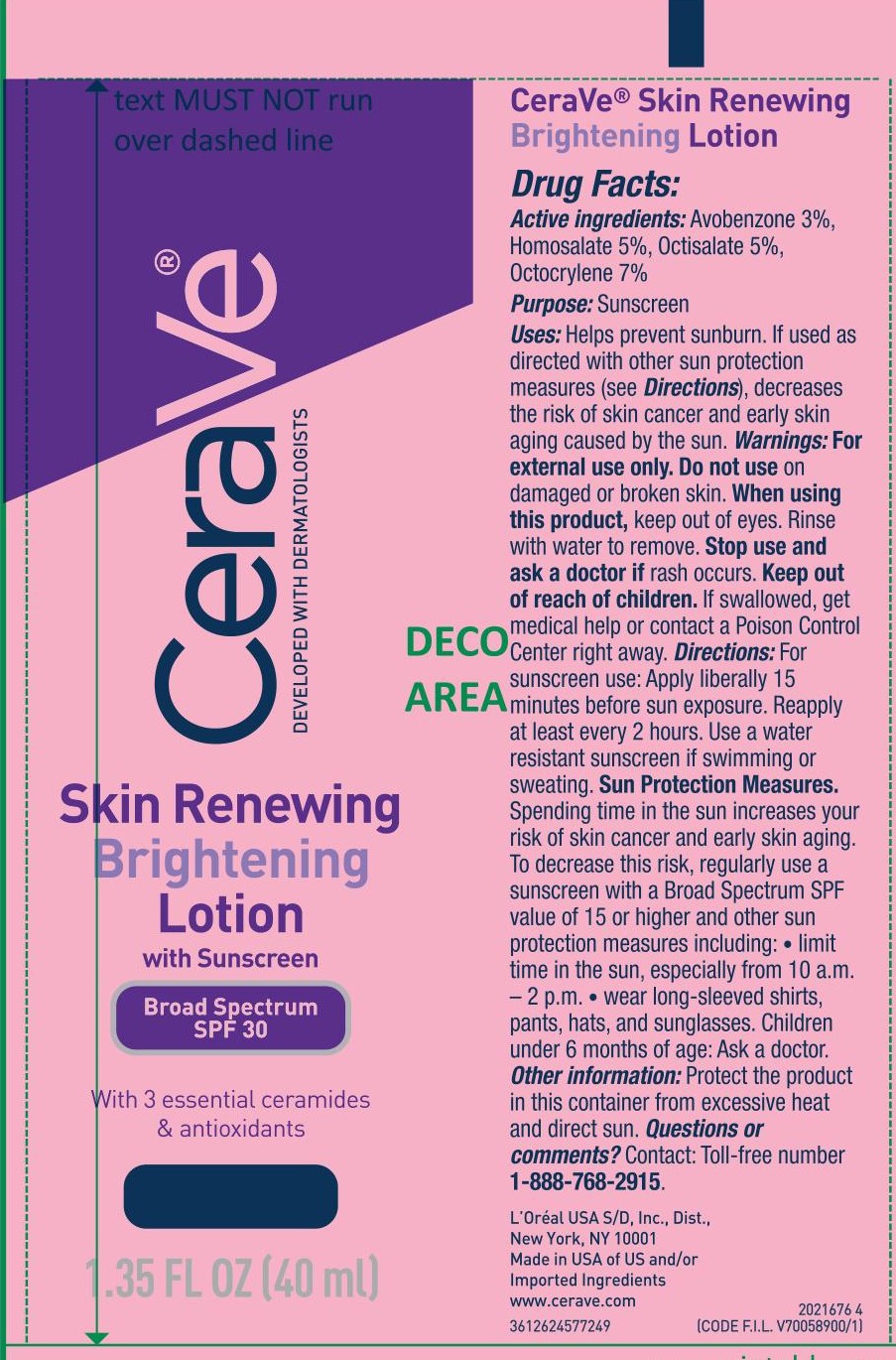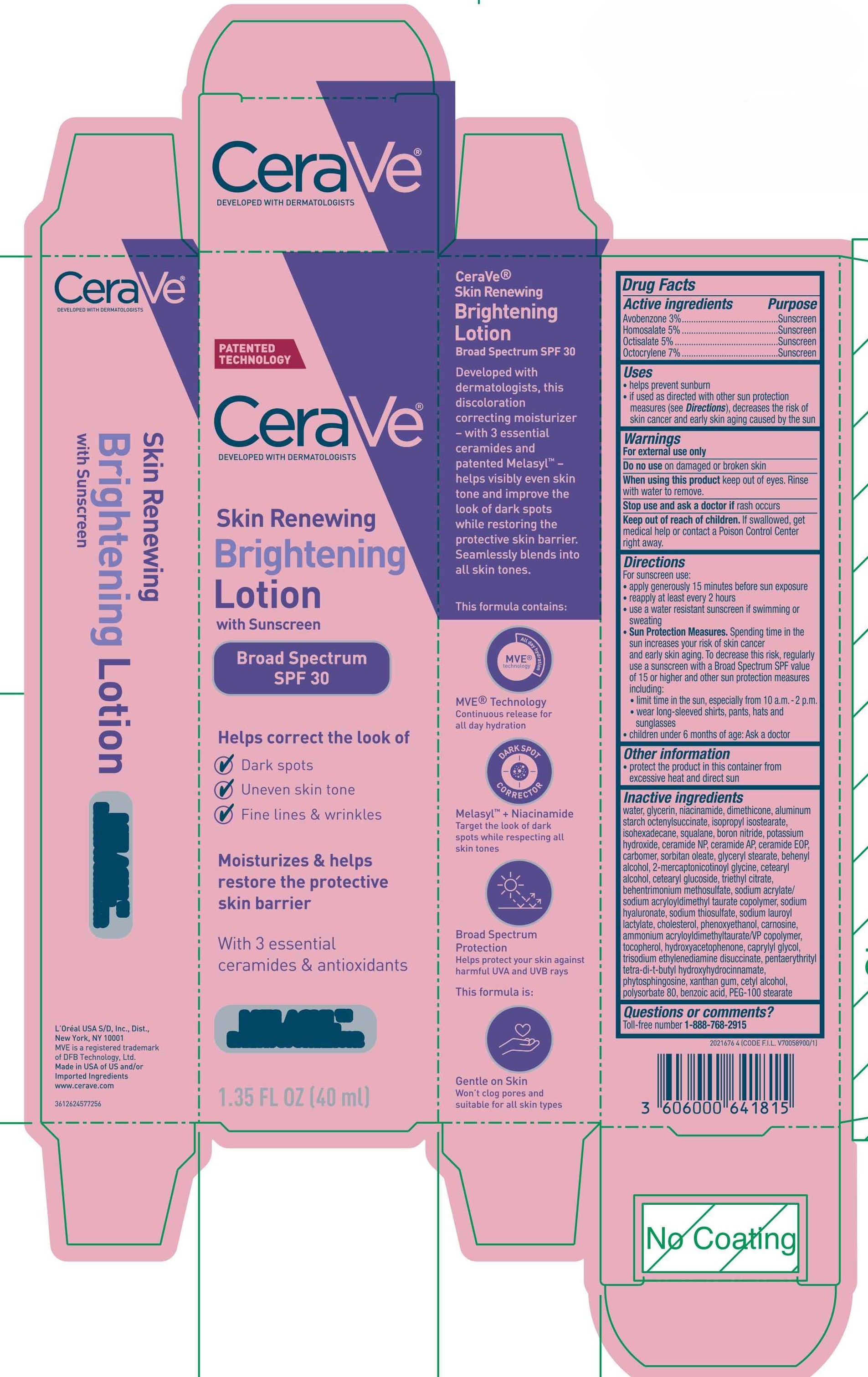 DRUG LABEL: CeraVe Developed with Dermatologists Skin Renewing Brightening with Sunscreen Broad Spectrum SPF 30
NDC: 49967-360 | Form: LOTION
Manufacturer: L'Oreal USA Products Inc
Category: otc | Type: HUMAN OTC DRUG LABEL
Date: 20251112

ACTIVE INGREDIENTS: AVOBENZONE 30 mg/1 mL; HOMOSALATE 50 mg/1 mL; OCTISALATE 50 mg/1 mL; OCTOCRYLENE 70 mg/1 mL
INACTIVE INGREDIENTS: WATER; GLYCERIN; NIACINAMIDE; DIMETHICONE; ALUMINUM STARCH OCTENYLSUCCINATE; ISOPROPYL ISOSTEARATE; ISOHEXADECANE; SQUALANE; BORON NITRIDE; POTASSIUM HYDROXIDE; CERAMIDE NP; CERAMIDE AP; CARBOMER; SORBITAN OLEATE; GLYCERYL STEARATE; BEHENYL ALCOHOL; CETEARYL ALCOHOL; CETEARYL GLUCOSIDE; TRIETHYL CITRATE; BEHENTRIMONIUM METHOSULFATE; SODIUM ACRYLATE/SODIUM ACRYLOYLDIMETHYLTAURATE COPOLYMER (4000000 MW); SODIUM HYALURONATE; SODIUM THIOSULFATE; SODIUM LAUROYL LACTYLATE; CHOLESTEROL; PHENOXYETHANOL; CARNOSINE; AMMONIUM ACRYLOYLDIMETHYLTAURATE/VP COPOLYMER; TOCOPHEROL; HYDROXYACETOPHENONE; CAPRYLYL GLYCOL; TRISODIUM ETHYLENEDIAMINE DISUCCINATE; PENTAERYTHRITYL TETRA-DI-T-BUTYL HYDROXYHYDROCINNAMATE; PHYTOSPHINGOSINE; XANTHAN GUM; CETYL ALCOHOL; POLYSORBATE 80; BENZOIC ACID; PEG-100 STEARATE

Drug Facts

Active ingredients

Avobenzone 3%

Homosalate 5%

Octisalate 5%

Octocrylene 7%

Purpose

Sunscreen

Uses

- helps prevent sunburn
- if used as directed with other sun protection measures (see Directions), decreases the risk of skin cancer and early skin aging caused by the sun

Warnings

For external use only

Do no use

on damaged or broken skin

When using this product

keep out of eyes. Rinse with water to remove.

Stop use and ask a doctor if

rash occurs

Keep out of reach of children.

If swallowed, get medical help or contact a Poison Control Center right away.

Directions

For sunscreen use:

- apply generously 15 minutes before sun exposure
- reapply at least every 2 hours
- use a water resistant sunscreen if swimming or sweating
- Sun Protection Measures. Spending time in the sun increases your risk of skin cancer and early skin aging. To decrease this risk, regularly use a sunscreen with a Broad Spectrum SPF value of 15 or higher and other sun protection measures including:
- limit time in the sun, especially from 10 a.m.-2 p.m.
- wear long-sleeved shirts, pants, hats and sunglasses
- children under 6 months of age: Ask a doctor

Other information

- protect the product in this container from excessive heat or direct sun

Inactive ingredients

water, glycerin, niacinamide, dimethicone, aluminum starch octenylsuccinate, isopropyl isostearate, isohexadecane, squalane, boron nitride, potassium hydroxide, ceramide NP, ceramide AP, ceramide EOP, carbomer, sorbitan oleate, glyceryl stearate, behenyl alcohol, 2-mercaptonicotinoyl glycine, cetearyl alcohol, cetearyl glucoside, triethyl citrate, behentrimonium methosulfate, sodium acrylate/ sodium acryloyldimethyl taurate copolymer, sodium hyaluronate, sodium thiosulfate, sodium lauroyl lactylate, cholesterol, phenoxyethanol, carnosine, ammonium acryloyldimethyltaurate/VP copolymer, tocopherol, hydroxyacetophenone, caprylyl glycol, trisodium ethylenediamine disuccinate, pentaerythrityl tetra-di-t-butyl hydroxyhydrocinnamate, phytosphingosine, xanthan gum, cetyl alcohol, polysorbate 80, benzoic acid, PEG-100 stearate

Questions or comments?

Toll-free number 1-888-768-2915